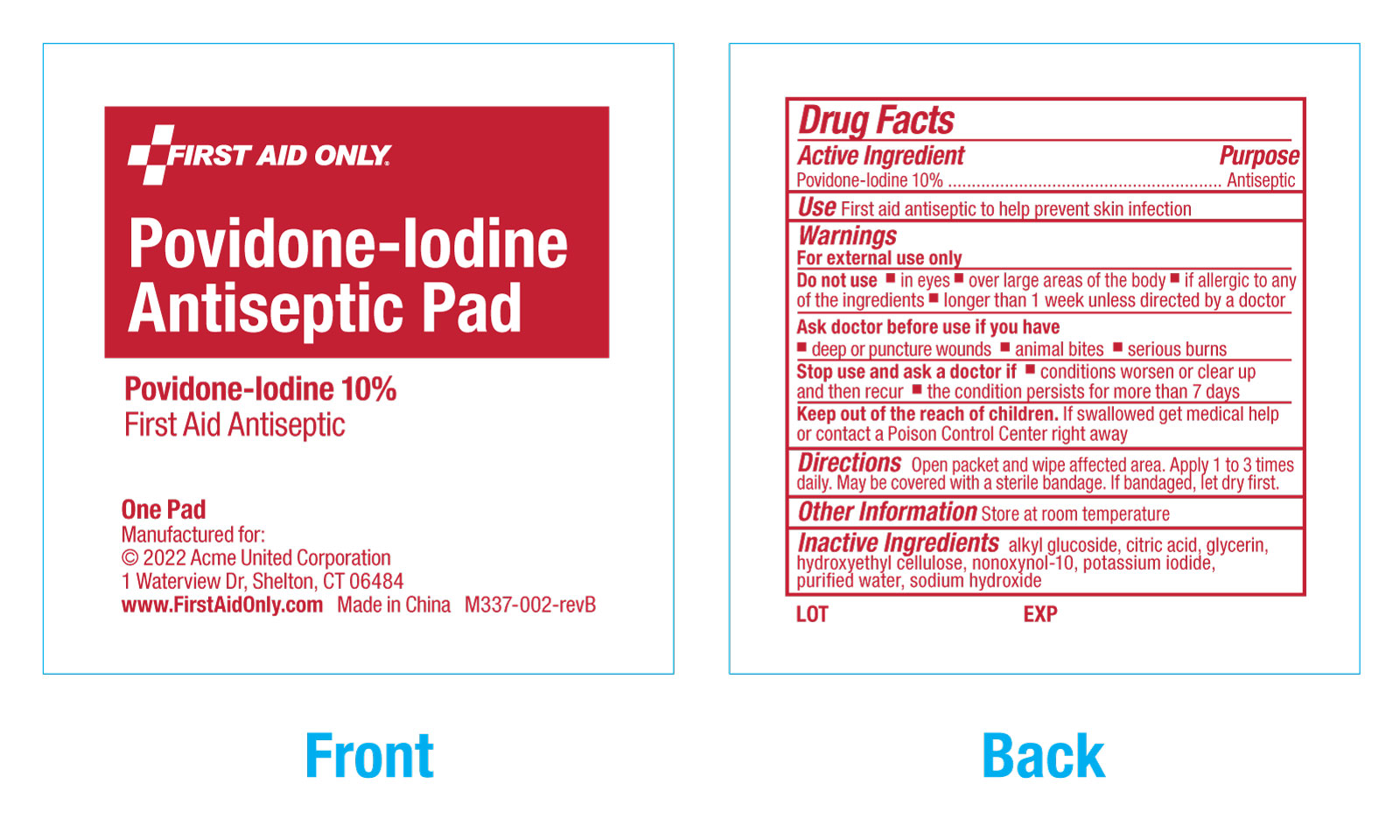 DRUG LABEL: First Aid Only Povidone-Iodine Antiseptic
NDC: 0924-8113 | Form: PATCH
Manufacturer: Acme United Corporation
Category: otc | Type: HUMAN OTC DRUG LABEL
Date: 20240813

ACTIVE INGREDIENTS: POVIDONE-IODINE 10 g/100 g
INACTIVE INGREDIENTS: NONOXYNOL-10; HYDROXYETHYL CELLULOSE, UNSPECIFIED; POTASSIUM IODIDE; SODIUM HYDROXIDE; GLYCERIN; CITRIC ACID MONOHYDRATE; WATER; C12-20 ALKYL GLUCOSIDE

First Aid Only Povidone-Iodine Antiseptic Pad

Active ingredient

Povidone-lodine 10%

Purpose

Antiseptic

Use

First aid antiseptic to help prevent skin infection

Warnings

For external use only

Do not use

▪ in eyes ▪ over large areas of the body ▪ if allergic to any of the ingredients

▪ longer than 1 week unless directed by a doctor

.

Ask a doctor before use if you have

▪ deep or puncture wounds ▪ animal bites ▪ serious burns

Stop use and ask a doctor if

▪ conditions worsen or clear up and then recur

▪ the condition persists for more than 7 days

Keep out of reach of children.

If swallowed get medical help or contact a Poison Control Center right away.

Driections

Open packet and wipe affected area. Apply 1 to 3 times daily. May be covered with a sterile bandage. If bandaged, let dry first.

Other information

Store at room temperature.

Inactive ingredients:

alkyl glucoside, citric acid, glycerin, hydroxyethyl cellulose, nonoxynol-10, potassium iodide,

purified water, sodium hydroxide

Pouch label